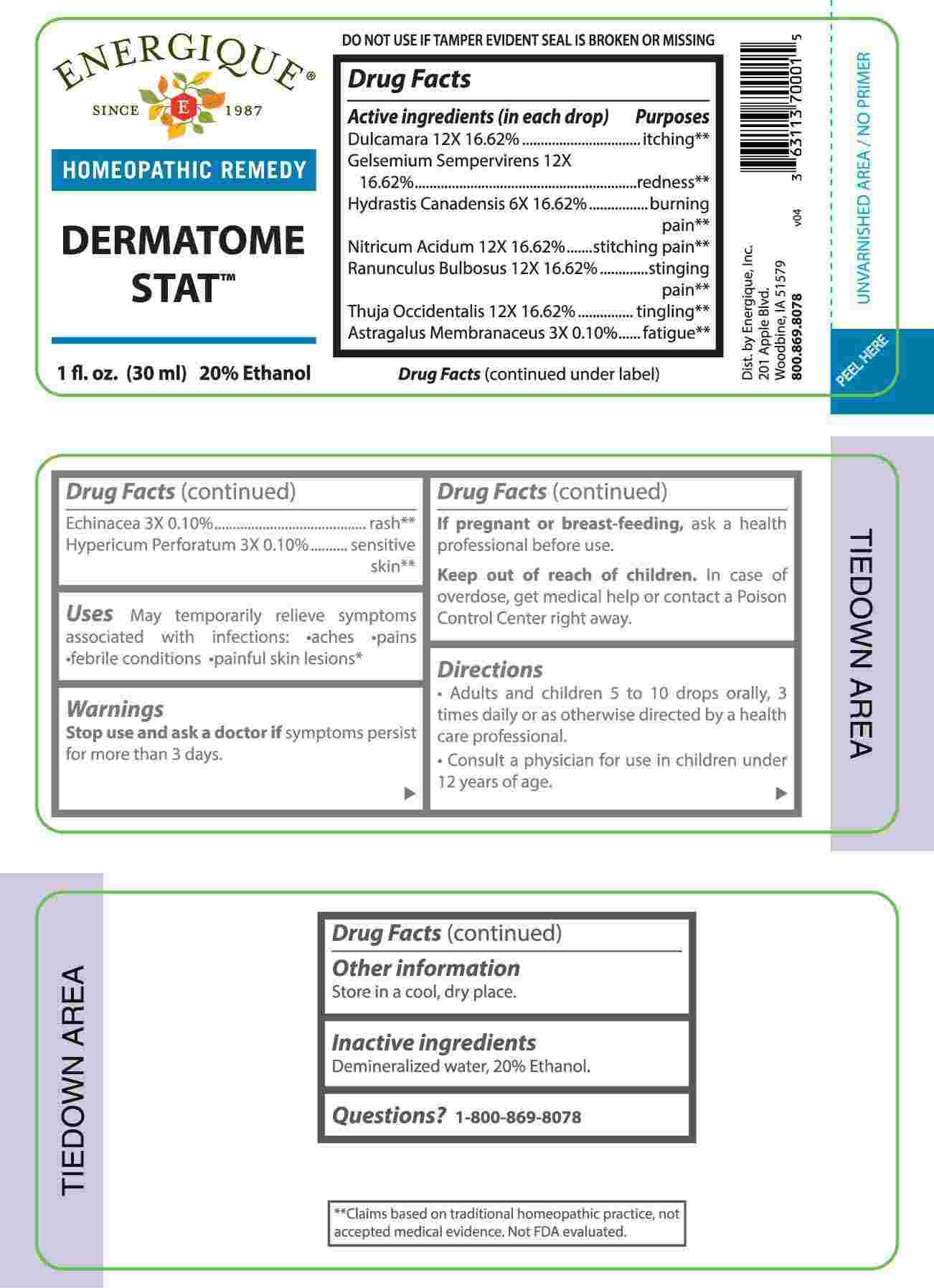 DRUG LABEL: DERMATOME STAT
NDC: 44911-0570 | Form: LIQUID
Manufacturer: Energique, Inc.
Category: homeopathic | Type: HUMAN OTC DRUG LABEL
Date: 20240820

ACTIVE INGREDIENTS: ASTRAGALUS PROPINQUUS ROOT 3 [hp_X]/1 mL; ECHINACEA ANGUSTIFOLIA WHOLE 3 [hp_X]/1 mL; HYPERICUM PERFORATUM WHOLE 3 [hp_X]/1 mL; GOLDENSEAL 6 [hp_X]/1 mL; SOLANUM DULCAMARA TOP 12 [hp_X]/1 mL; GELSEMIUM SEMPERVIRENS ROOT 12 [hp_X]/1 mL; NITRIC ACID 12 [hp_X]/1 mL; RANUNCULUS BULBOSUS WHOLE 12 [hp_X]/1 mL; THUJA OCCIDENTALIS LEAFY TWIG 12 [hp_X]/1 mL
INACTIVE INGREDIENTS: WATER; ALCOHOL

DRUG FACTS:

ACTIVE INGREDIENTS:

(in each drop): Dulcamara 12X 16.62%, Gelsemium Sempervirens 12X 16.62%, Hydrastis Canadensis 6X 16.62%, Nitricum Acidum 12X 16.62%, Ranunculus Bulbosus 12X 16.62%, Thuja Occidentalis 12X 16.62%, Astragalus Membranaceus 3X 0.10%, Echinacea (Angustifolia) 3X 0.10%, Hypericum Perforatum 3X 0.10%.

PURPOSE:

Dulcamara - itching,** Gelsemium Sempervirens - redness,** Hydrastis Canadensis – burning pain,** Nitricum Acidum – stitching pain,** Ranunculus Bulbosus – stinging pain,** Thuja Occidentalis – tingling,** Astragalus Membranaceus - fatigue,** Echinacea - rash,** Hypericum Perforatum – sensitive skin**

**Claims based on traditional homeopathic practice, not accepted medical evidence. Not FDA evaluated.

USES:

May temporarily relieve symptoms associated with infections:

• aches • pains • febrile conditions • painful skin lesions**

**Claims based on traditional homeopathic practice, not accepted medical evidence. Not FDA evaluated.

WARNINGS:

Stop use and ask a doctor if symptoms persist for more than 3 days.

If pregnant or breastfeeding, ask a health professional before use.

Keep out of reach of children. In case of overdose, get medical help or contact a Poison Control Center right away.

DO NOT UE IF TAMPER EVIDENT SEAL IS BROKEN OR MISSING

Store in a cool, dry place.

KEEP OUT OF REACH OF CHILDREN:

In case of overdose, get medical help or contact a Poison Control Center right away.

DIRECTIONS:

• Adults and children 5 to 10 drops orally, 3 times daily or as otherwise directed by a health care professional.

• Consult a physician for use in children under 12 years of age.

INACTIVE INGREDIENTS:

Demineralized water, 20% Ethanol.

QUESTIONS:

Dist. by Energique, Inc.
201 Apple Blvd.
Woodbine, IA 51579

800.869.8078

PACKAGE LABLE DISPLAY:

ENERGIQUE

SINCE 1987

HOMEOPATHIC REMEDY

DERMATOME STAT

1 fl. oz. (30 ml)